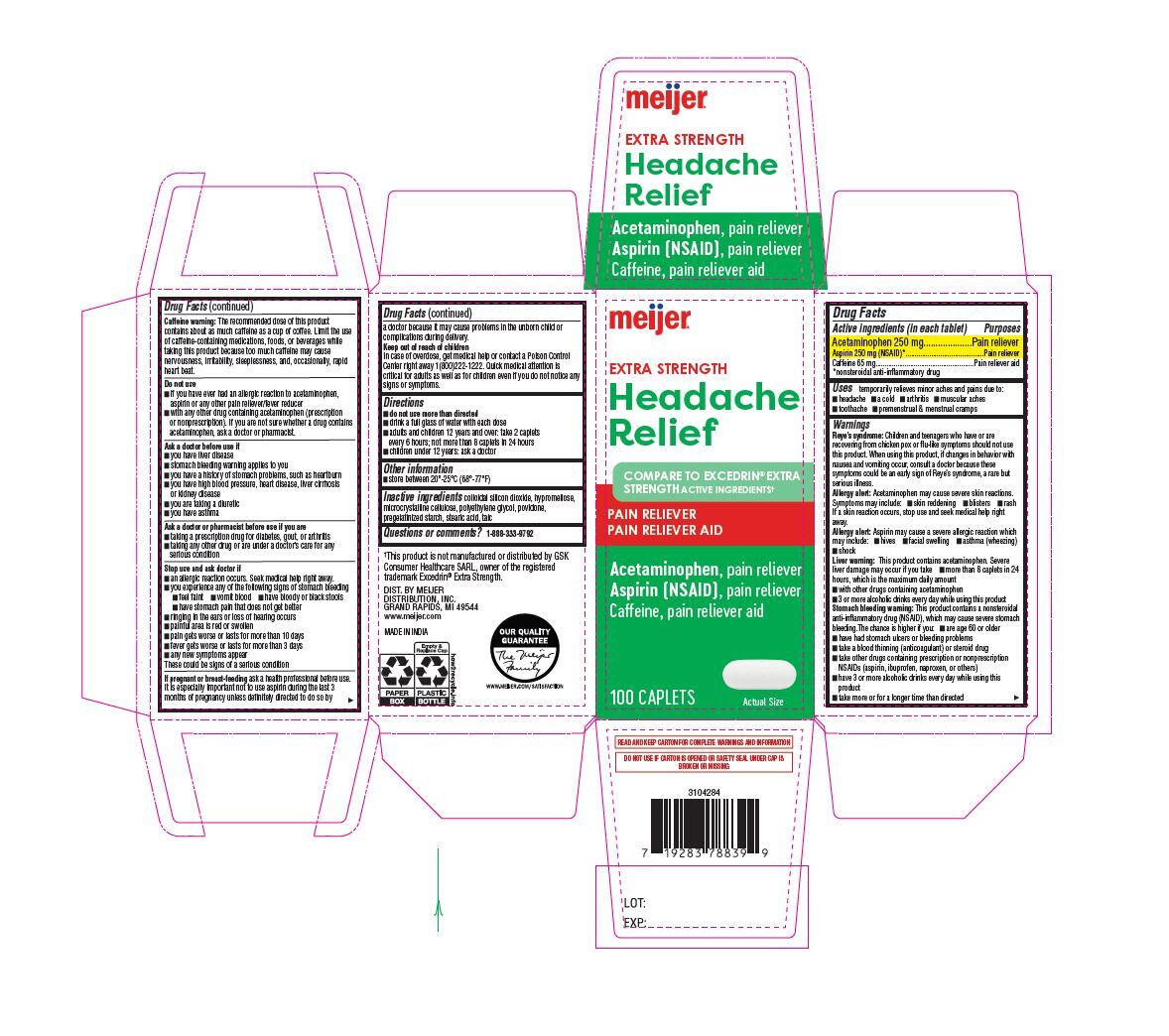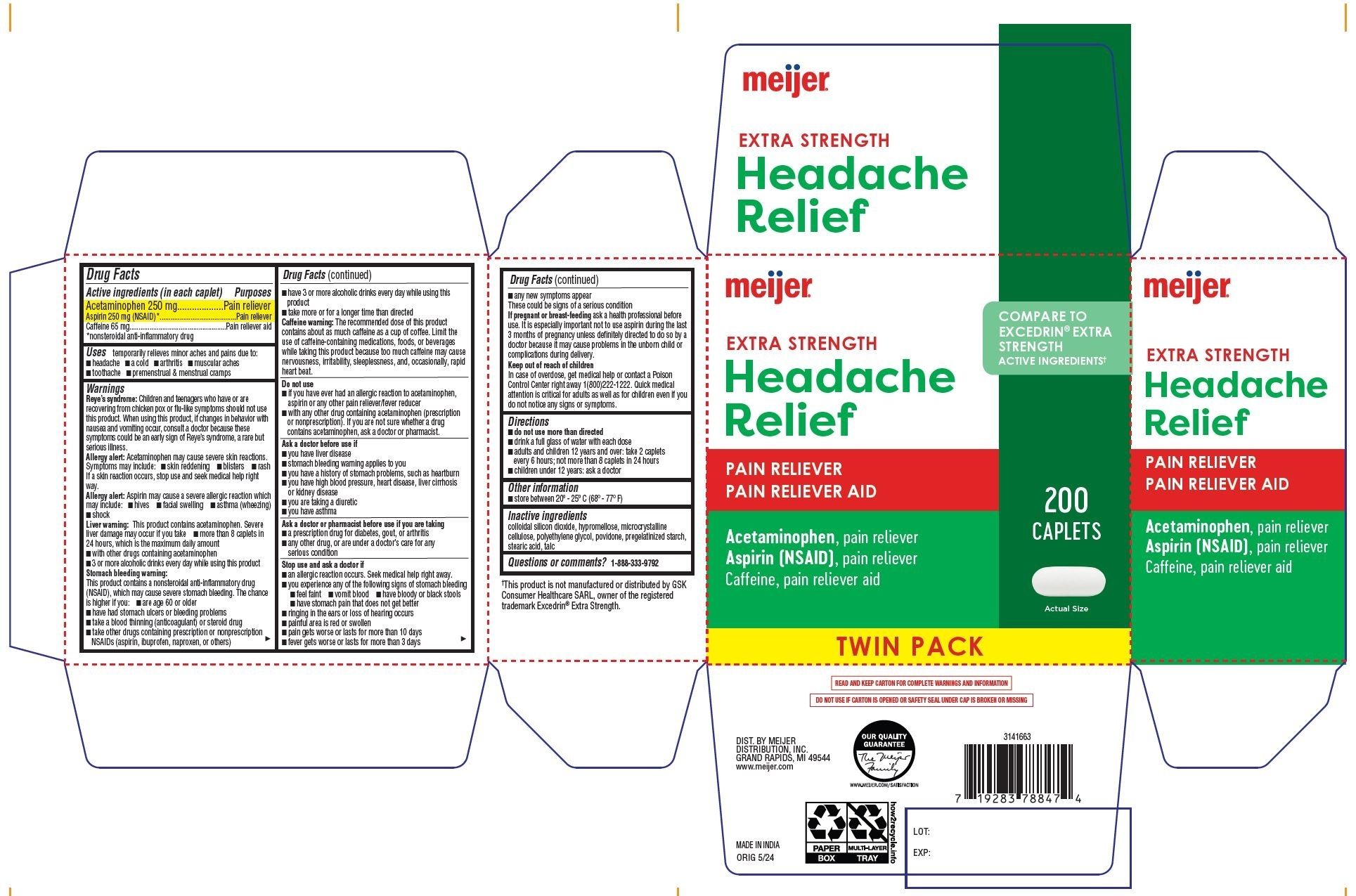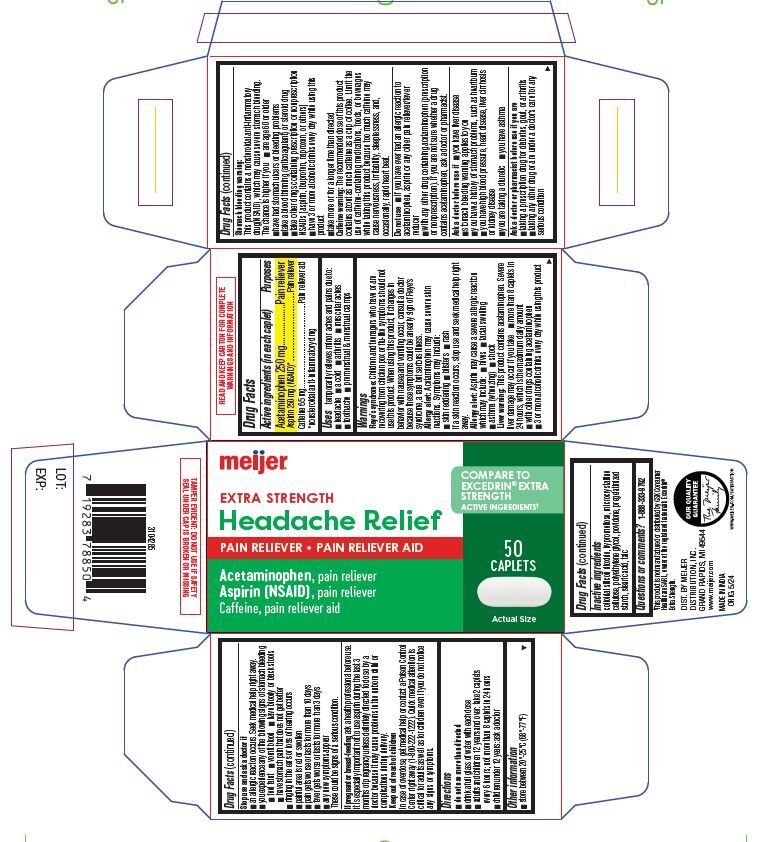 DRUG LABEL: EXTRA STRENGTH HEADACHE RELIEF
NDC: 79481-0062 | Form: TABLET
Manufacturer: Meijer, Inc.
Category: otc | Type: HUMAN OTC DRUG LABEL
Date: 20241220

ACTIVE INGREDIENTS: ACETAMINOPHEN 250 mg/1 1; ASPIRIN 250 mg/1 1; CAFFEINE 65 mg/1 1
INACTIVE INGREDIENTS: SILICON DIOXIDE; HYPROMELLOSE, UNSPECIFIED; MICROCRYSTALLINE CELLULOSE; POLYETHYLENE GLYCOL, UNSPECIFIED; POVIDONE; STARCH, CORN; STEARIC ACID; TALC

EXTRA STRENGTH HEADACHE RELIEF